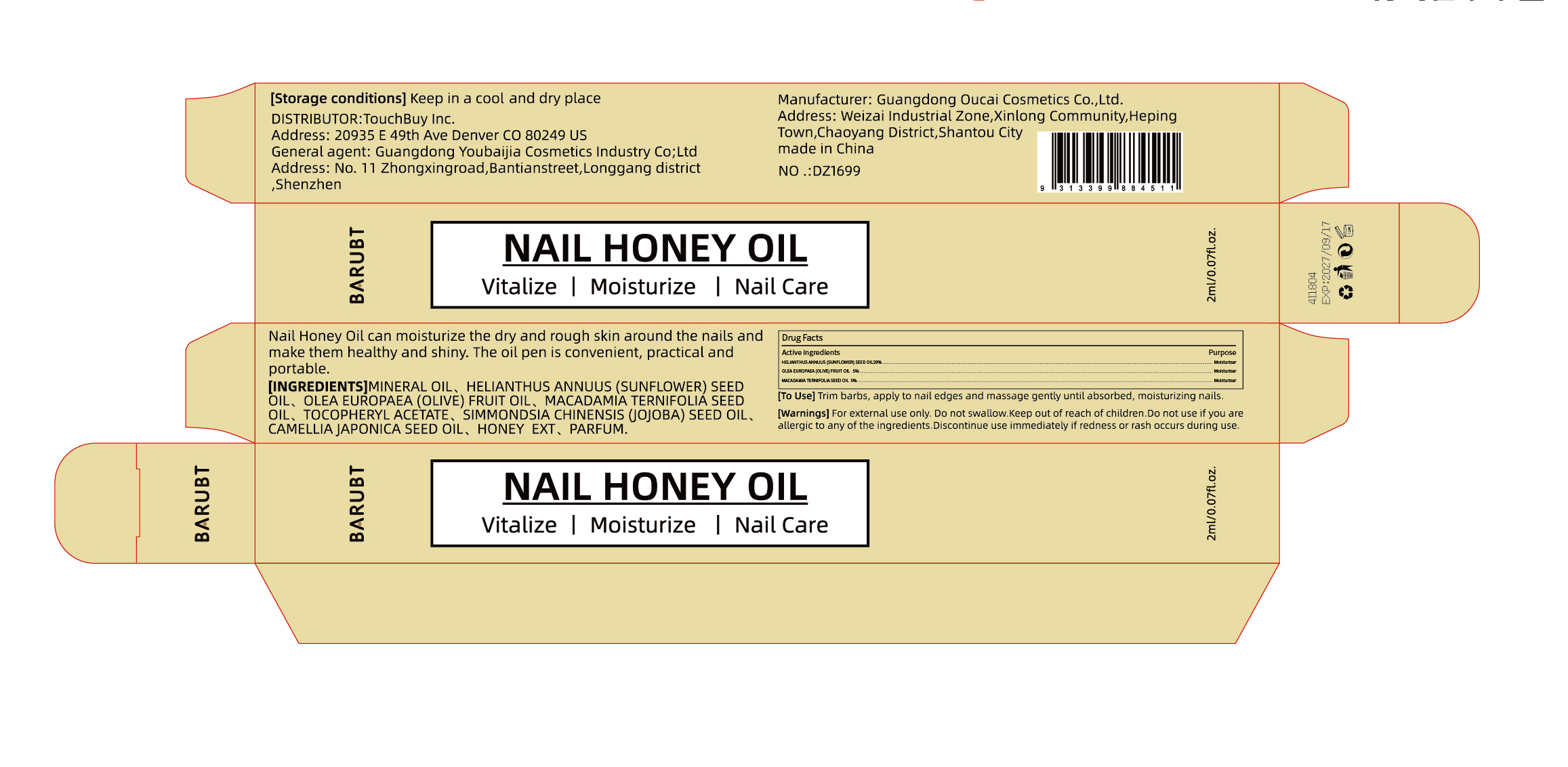 DRUG LABEL: BARUBT Nail Honey Oil
NDC: 84712-028 | Form: OIL
Manufacturer: Guangdong Youbaijia Cosmetic Industry Co., Ltd
Category: otc | Type: HUMAN OTC DRUG LABEL
Date: 20241028

ACTIVE INGREDIENTS: MACADAMIA TERNIFOLIA SEED OIL 0.1 g/2 mL; HELIANTHUS ANNUUS (SUNFLOWER) SEED OIL 0.4 g/2 mL; OLEA EUROPAEA (OLIVE) FRUIT OIL 0.1 g/2 mL
INACTIVE INGREDIENTS: MINERAL OIL 1.358 g/2 mL

ACTIVE INGREDIENT

HELIANTHUS ANNUUS (SUNFLOWER) SEED OIL 20%
OLEA EUROPAEA (OLIVE) FRUIT OIL 5%
MACADAMIA TERNIFOLIA SEED OIL 5%

Do not use if you areallergic to any of the ingredients

Keep away from children. Do not swallow.

PURPOSE

moisturize the dry and rough skin around the nails

QUESTIONS

Contact name: Jessie Peng
Company phone number: +1 818 579 7288
Company e-mail: jessie@registeragentllc.com

STOP USE

Discontinue use immediately if redness or rash occurs during use.

WARNINGS

for external use only

WHEN USING

keep out of eyes. Rinse with water to remove.

INACTIVE INGREDIENT

MINERAL OIL
TOCOPHERYL ACETATE
SIMMONDSIA CHINENSIS (JOJOBA) SEED OIL
CAMELLIA JAPONICA SEED OIL
Honey ext
PARFUM

STORAGE AND HANDLING

Storage conditions:Keep away from light and in a dry place.

DOSAGE AND ADMINISTRATION

[To Use] Trim barbs, apply to nail edges and massage gently until absorbed, moisturizing nails.

INDICATIONS AND USAGE

Nail Honey Oil can moisturize the dry and rough skin around the nails and make them healthy and shiny. The oil pen is convenient, practical and portable.